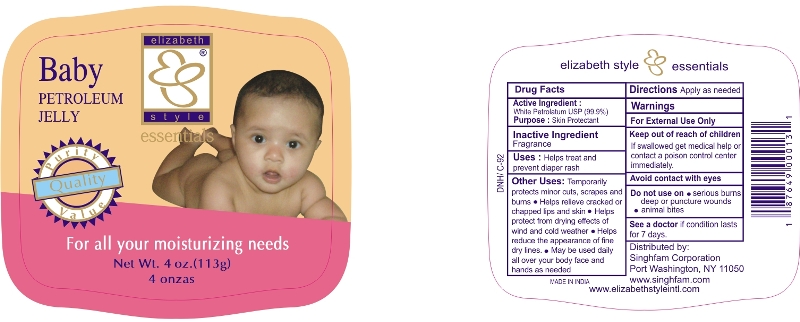 DRUG LABEL: Baby Petroleum
NDC: 52920-126 | Form: JELLY
Manufacturer: Singhfam Corporation
Category: otc | Type: HUMAN OTC DRUG LABEL
Date: 20121004

ACTIVE INGREDIENTS: PETROLATUM 0.99 g/1 g

Active Ingredient

White Petrolatum USP (99.9 %)

Purpose

Skin Protectant

Inactive Ingredient

Fragrance

Uses

Helps treat and prevent diaper rash.

Other Uses:

Temporarily protects minor cuts, scrapes and burns

- Helps relieve cracked or chapped lips and skin
- Helps protect from drying effects of wind and cold weather
- Helps reduce the appearance of fine dry lines
- May be used daily all over your body face and hands as needed

Directions

Apply as needed

Warnings

For External Use Only.

Keep out of reach of children

If swallowed get medical help or contact a poison control center immediately

Avoid contact with eyes

Do not use on

- serious burns
- deep or puncture wounds
- animal bites

See a doctor

if condition lasts for 7 days

PACKAGE LABEL

PRINCIPAL DISPLAY PANEL
Baby Petroleum Jelly
For all your moisturizing needs
Net Wt. 4 oz. (113 g)
4 onzas